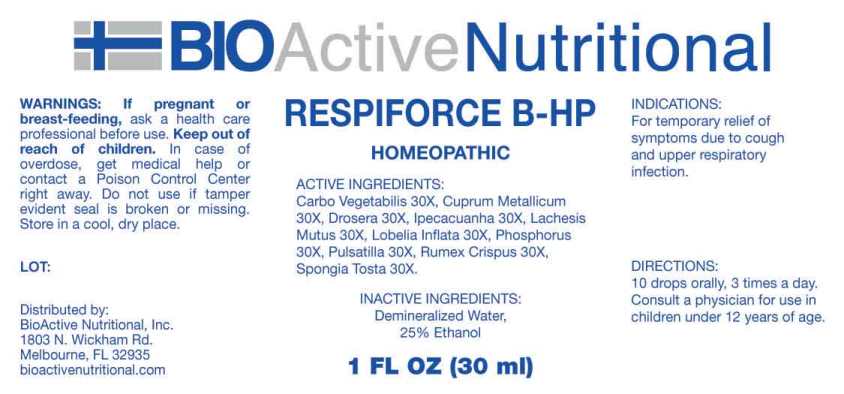 DRUG LABEL: Respiforce
NDC: 43857-0623 | Form: LIQUID
Manufacturer: BioActive Nutritional, Inc.
Category: homeopathic | Type: HUMAN OTC DRUG LABEL
Date: 20240912

ACTIVE INGREDIENTS: ACTIVATED CHARCOAL 30 [hp_X]/1 mL; COPPER 30 [hp_X]/1 mL; DROSERA ROTUNDIFOLIA WHOLE 30 [hp_X]/1 mL; IPECAC 30 [hp_X]/1 mL; LACHESIS MUTA VENOM 30 [hp_X]/1 mL; LOBELIA INFLATA WHOLE 30 [hp_X]/1 mL; PHOSPHORUS 30 [hp_X]/1 mL; PULSATILLA VULGARIS WHOLE 30 [hp_X]/1 mL; RUMEX CRISPUS ROOT 30 [hp_X]/1 mL; SPONGIA OFFICINALIS SKELETON, ROASTED 30 [hp_X]/1 mL
INACTIVE INGREDIENTS: WATER; ALCOHOL

DRUG FACTS:

ACTIVE INGREDIENTS:

Carbo Vegetabilis 30X, Cuprum Metallicum 30X, Drosera (Rotundifolia) 30X, Ipecacuanha 30X, Lachesis Mutus 30X, Lobelia Inflata 30X, Phosphorus 30X, Pulsatilla (Vulgaris) 30X, Rumex Crispus 30X, Spongia Tosta 30X

INDICATIONS:

For temporary relief of symptoms due to cough and upper respiratory infection.

WARNINGS:

If pregnant or breast-feeding, ask a health care professional before use.

Keep out of reach of children. In case of overdose, get medical help or contact a Poison Control Center right away.

Do not use if tamper evident seal is broken or missing.

Store in cool, dry place.

KEEP OUT OF REACH OF CHILDREN:

In case of overdose, get medical help or contact a Poison Control Center right away.

DIRECTIONS:

10 drops orally, 3 times a day. Consult a physician for use in children under 12 years of age.

INDICATIONS AND USAGE:

For temporary relief of symptoms due to cough and upper respiratory infection.

INACTIVE INGREDIENTS:

Demineralized Water, 25% Ethanol

QUESTIONS:

Distributed by:
BioActive Nutritional, Inc.
1803 N. Wickham Rd.
Melbourne, FL 32935
bioactivenutritional.com

PACKAGE LABEL DISPLAY:

BIOActiveNutritional

RESPIFORCE B-HP

HOMEOPATHIC

1 FL OZ (30 ml)